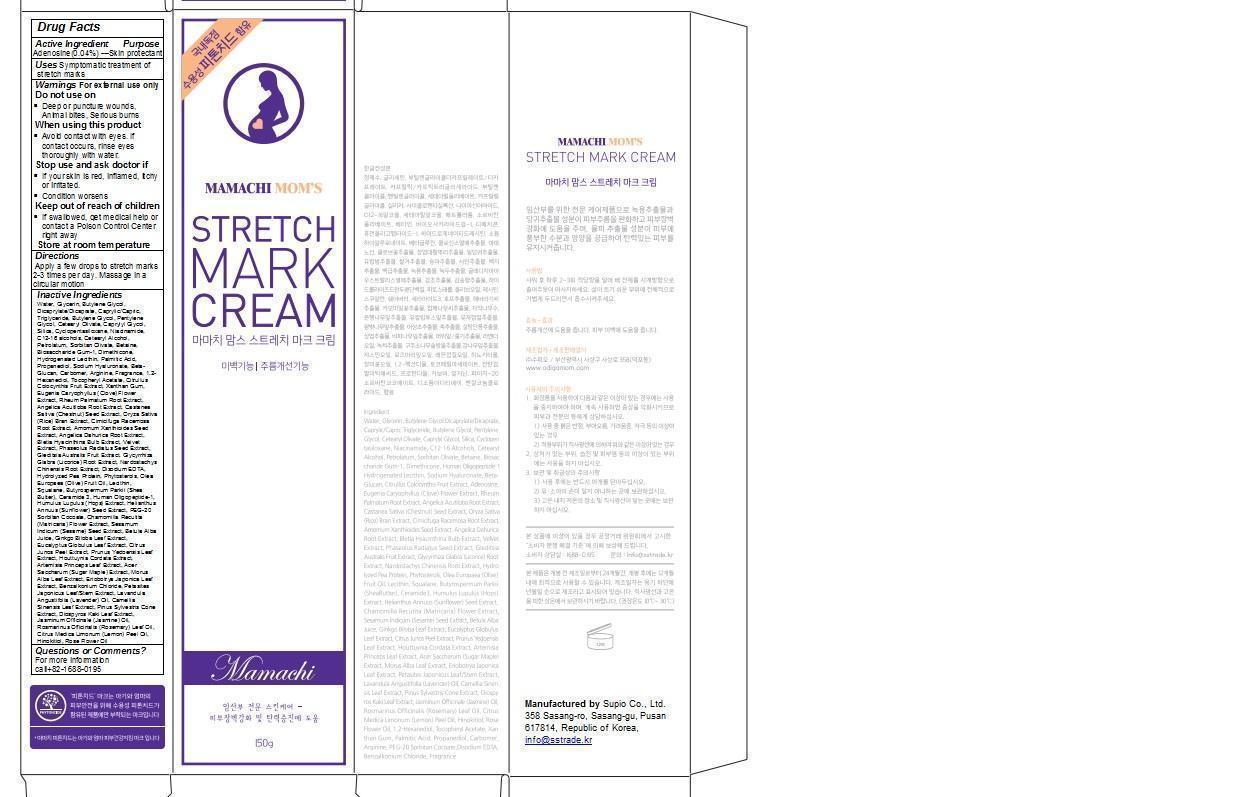 DRUG LABEL: MAMACHI MOMS STRETCH MARK CREAM
NDC: 63219-100 | Form: CREAM
Manufacturer: Supio Co,. Ltd.
Category: otc | Type: HUMAN OTC DRUG LABEL
Date: 20140418

ACTIVE INGREDIENTS: adenosine 6 g/150 g
INACTIVE INGREDIENTS: Water; Glycerin; Butylene Glycol Dicaprylate/Dicaprate; Pentylene Glycol; Cetearyl Olivate; Caprylyl Glycol; Niacinamide; C12-16 alcohols; Petrolatum; Sorbitan Olivate; CAPRYLIC/CAPRIC/LAURIC TRIGLYCERIDE; Butylene Glycol; Betaine; Dimethicone; HYDROGENATED SOYBEAN LECITHIN; PALMITIC ACID; Propanediol; HYALURONATE SODIUM; Arginine; Hexanediol; .ALPHA.-TOCOPHEROL ACETATE; CITRULLUS COLOCYNTHIS FRUIT; XANTHAN GUM; EUGENIA UNIFLORA WHOLE; RHEUM PALMATUM ROOT; ANGELICA ACUTILOBA ROOT; ORYZA SATIVA WHOLE; ACTAEA CIMICIFUGA ROOT; AMOMUM VILLOSUM VAR. XANTHIOIDES WHOLE; ANGELICA DAHURICA ROOT; DISODIUM (ETHOXYCARBONYL)PHOSPHONATE; OLEA EUROPAEA FRUIT VOLATILE OIL; LECITHIN, SOYBEAN; Squalane; Shea Butter; CERAMIDE 3; HUMULUS LUPULUS WHOLE

MAMACHI MOM’S STRETCH MARK CREAM